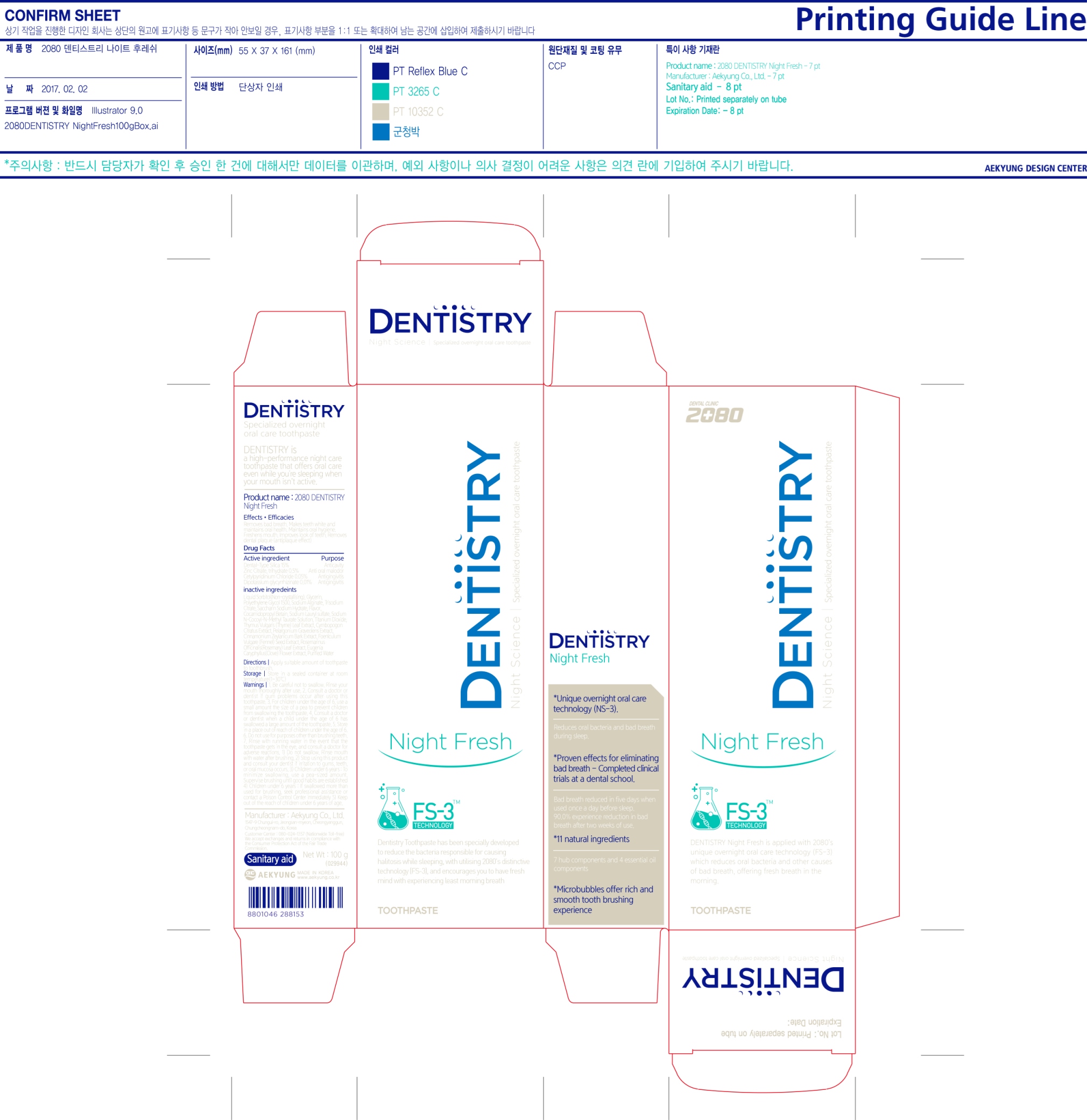 DRUG LABEL: 2080 Dentistry Night Fresh
NDC: 67225-0009 | Form: PASTE, DENTIFRICE
Manufacturer: Aekyung Industrial Co., Ltd.
Category: otc | Type: HUMAN OTC DRUG LABEL
Date: 20170203

ACTIVE INGREDIENTS: SILICON DIOXIDE 15 g/100 g
INACTIVE INGREDIENTS: CETYLPYRIDINIUM CHLORIDE; ZINC CITRATE TRIHYDRATE; GLYCYRRHIZINATE DIPOTASSIUM; SORBITOL; GLYCERIN; POLYETHYLENE GLYCOL 1500; SODIUM ALGINATE; SODIUM CITRATE; SACCHARIN SODIUM; COCAMIDOPROPYL BETAINE; SODIUM LAURYL SULFATE; SODIUM METHYL COCOYL TAURATE; TITANIUM DIOXIDE; THYMUS VULGARIS LEAF; CYMBOPOGON CITRATUS WHOLE; PELARGONIUM GRAVEOLENS WHOLE; CINNAMON BARK OIL; FENNEL SEED; ROSEMARY; CLOVE; WATER

Drug Facts

ACTIVE INGREDIENT

Active Ingredients | Purpose
Dental-Type Silica 15% | Anticavity
Zinc Citrate, trihydrate 0.5% | Anti Oral Malodor
Cetylpyridinium Chloride 0.05% | Antigingivitis
Dipotassium Glycyrrhizinate 0.01% | Antigingivitis

WARNINGS

Be careful not to swallow. Rinse your mouth thoroughly after use. Consult a doctor or dentist if gum problems occur after using this toothpaste.

KEEP OUT OF REACH OF CHILDREN

Keep out of the reach of children under 6 years of age

STOP USE

Stop using this product and consult your dentist if irritation to gums, teeth, or oral mucosa occurs

DOSAGE AND ADMINISTRATION

Do not swallow. Rinse mouth with water after brushing.

Children under 6 years:

- To minimize swallowing, use a pea-sized amount. Supervise brushing until good habits are established.

- If swallowed more than used for brushing, seek professional assistance or contact a Poison Control Center immediately.

INDICATIONS AND USAGE

- Removes bad breath

- Maintains oral health

INSTRUCTIONS FOR USE

Directions: Apply suitable amount of toothpaste to toothbrush

Do not use for purpose other than brushing teeth. Rinse with running water in the event that the toothpaste gets in the eye and consult a doctor for adverse reactions

STORAGE AND HANDLING

Store in a sealed container at room temperature {1~30°C}

QUESTIONS

Customer Center: 080-024-1357 (Nationwide Toll-Free)

We accept exchanges and returns in compliance with the Consumer Protection Act of the Fair Trade Commission

www.aekyung.co.kr

Manufacturer: Aekyung Co., Ltd

1547-9 Chungui-ro, Jeongsan-myeon, Cheongyanggun, Chungcheongnam-do, Korea

INACTIVE INGREDIENT

Inactive Ingredients: Liquid Sorbitol (Non-crystalizing), Glycerin, Polyethylene Glycol 1500, Sodium Alginate, Trisodium Citrate, Saccharin Sodium Hydrate, Cocamidopropyl Betain, Sodium Lauryl Sulfate, Sodium N-Cocoyl-N-Methyl Taurate Solution, Titanium Dioxide, Thymus Vulgaris (Thyme) Leaf Extract, Cymbopogon Citratus Extract, Pelargonium Graveolens Extract, Cinnamonium Zeylanicum Bark Extract, Foenlculum Vulgare (Fennel) Seed Extract, Rosemarinus Officinalis (Rosemary) Leaf Extract, Eugenia Caryphyllus (Clove) Flower Extract, Purified Water